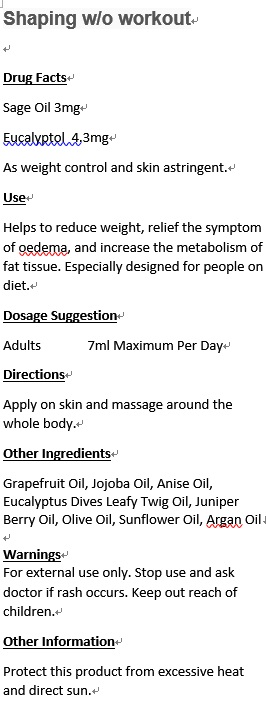 DRUG LABEL: Stork I Synergy
NDC: 70470-1224 | Form: OIL
Manufacturer: PHYTOPIA CO., LTD.
Category: otc | Type: HUMAN OTC DRUG LABEL
Date: 20180110

ACTIVE INGREDIENTS: SAGE OIL 5 mg/50 mL
INACTIVE INGREDIENTS: BERGAMOT OIL 15 mg/50 mL; BLACK PEPPER OIL 0.37 mL/50 mL; GINGER OIL 2 mg/50 mL; SANDALWOOD OIL 10 mg/50 mL; JOJOBA OIL 6 mL/50 mL; OLIVE OIL 21 mL/50 mL; SUNFLOWER OIL 7.8 mL/50 mL; ARGAN OIL 7 mL/50 mL

Drug Facts

Sage Oil 3mg

Eucalyptol 4.3mg

As Weight Control And Skin Astringent.

Use

Helps to reduce weight, relief the symptom of oedema, and increase the metabolism of fat tissue. Especially designed for people on diet.

Dosage Suggestion

Adults 7ml Maximum Per Day

Directions

Apply on skin and massage around the whole body.

INACTIVE INGREDIENT

Other Ingredients

Grapefruit Oil, Jojoba Oil, Anise Oil, Eucalyptus Dives Leafy Twig Oil, Juniper Berry Oil, Olive Oil, Sunflower Oil, Argan Oil

Warnings

For external use only. Stop use and ask doctor if rash occurs. Keep out of reach of children.

Warnings

For external use only. Stop use and ask doctor if rash occurs. Keep out of reach of children.

Other Information

Protect this product from excessive heat and direct sun.

PACKAGE LABEL

Shaping w/o Workout